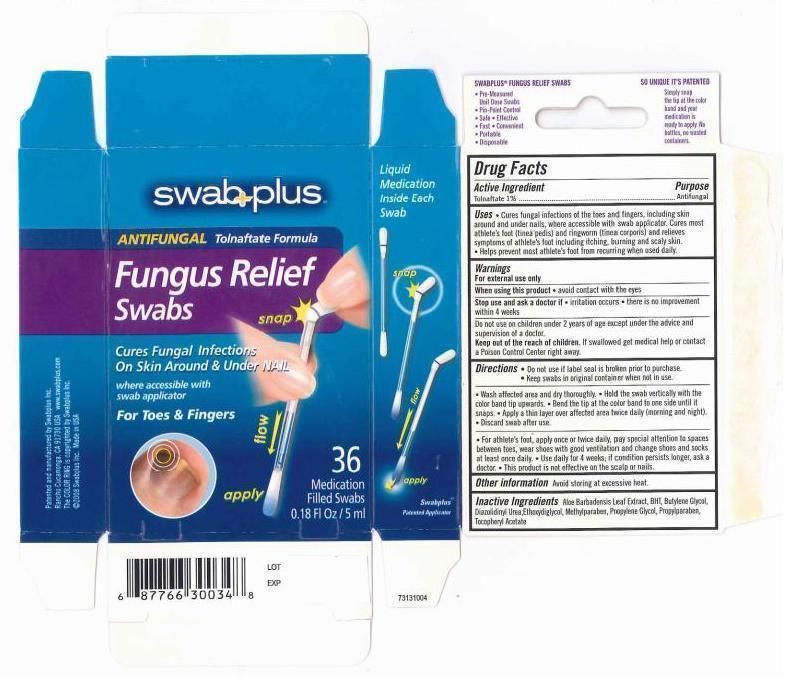 DRUG LABEL: Fungus Relief                                                                                                 
NDC: 65734-348 | Form: SOLUTION
Manufacturer: Swabplus Inc.
Category: otc | Type: HUMAN OTC DRUG LABEL
Date: 20150128

ACTIVE INGREDIENTS: TOLNAFTATE 10 mg/1 mL
INACTIVE INGREDIENTS: ALOE VERA LEAF; BUTYLATED HYDROXYTOLUENE; BUTYLENE GLYCOL; DIAZOLIDINYL UREA; DIETHYLENE GLYCOL MONOETHYL ETHER; METHYLPARABEN; PROPYLENE GLYCOL; PROPYLPARABEN

Fungus Relief Swab

Drug Facts

Active Ingredient

Tolnaftate 1%

Purpose

Antifungal

Uses

- Cures fungal infections of the toes and fingers, including skin around and under nails, where accessible with swab applicator. Cures most athlete's foot (tinea pedis) and ringworm (tinea corporis) and relieves symptoms of athlete's foot including itching, burning and scaly skin.
- Help prevent most athlete's foot from recuring when uses daily.

Warings

For external use only.
When using this product avoid contact with eyes.
Stop use and ask a doctor if irritation occurs. there is no improvement within 4 weeks.
Do not use on children under 2 years of age except under the advice and supervision of a doctor.

Keep out of the reach of children

If swallowed get medical help or contact a Poison Control Center right away.

Directions

- Do not use if label seal is broken prior to purchase.
- Keep swabs in original container when not in use.
- wash affected area and dry thoroughly.
- Hold the swab vertically with the color band tip upwards.
- Bend the tip at the color band to one side until it snaps.
- Apply a thin layer over affected area twice daily (morning and night)
- Discard swab after use.
- For athlete's foot, apply once or twice daily, pay special attention to spaces between toes, wear shoes with good ventilation and change shoes and socks at least once daily.
- Use daily for 4 weeks; if condition persists longer, ask a doctor.
- This product is not effective on the scalp or nails.

Other information

Avoid storing at excessive heat.

Inactive Ingredients

Aloe Barbadensis Leaf Extract. BHT. Butylene Glycol, Diazolidinyl Urea, Ethoxydiglycol, Methylparaben, Propylene Glycol, Propylparaben. Tocopheryl Acetate

Image of carton label